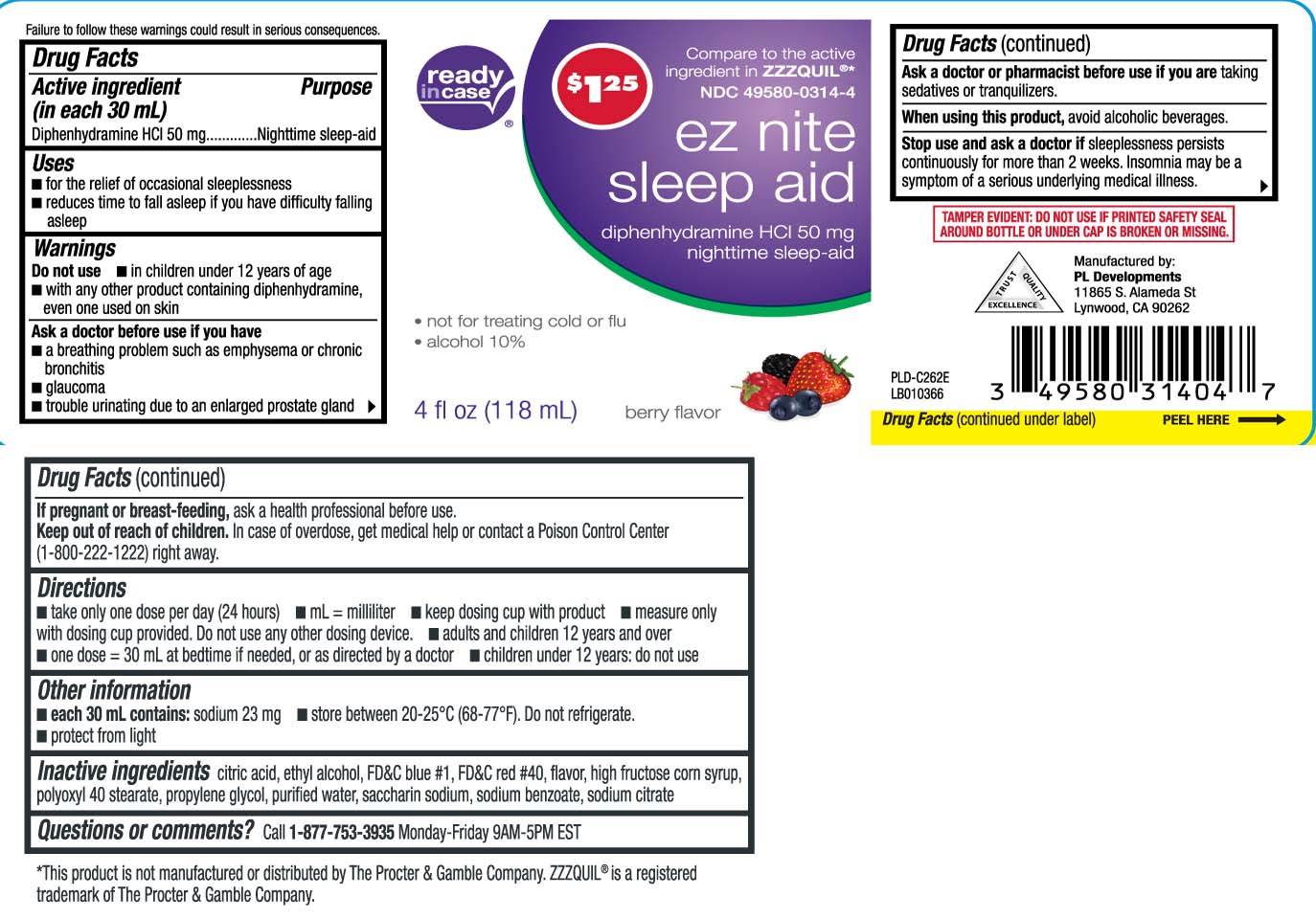 DRUG LABEL: Sleep Aid
NDC: 49580-0314 | Form: LIQUID
Manufacturer: P & L Development, LLC
Category: otc | Type: HUMAN OTC DRUG LABEL
Date: 20250324

ACTIVE INGREDIENTS: DIPHENHYDRAMINE HYDROCHLORIDE 50 mg/30 mL
INACTIVE INGREDIENTS: ANHYDROUS CITRIC ACID; PROPYLENE GLYCOL; POLYOXYL 40 STEARATE TYPE I; WATER; SODIUM BENZOATE; SACCHARIN SODIUM ANHYDROUS; HIGH FRUCTOSE CORN SYRUP; FD&C BLUE NO. 1; ALCOHOL; FD&C RED NO. 40; SODIUM CITRATE

Drug Facts

Active ingredient (in each 30 mL)

Diphenhydramine HCl 50 mg

Purpose

Nighttime sleep-aid

Uses

- for the relief of occasional sleeplessness
- reduces time to fall asleep if you have difficulty falling asleep

Warnings

Do not use

- in children under 12 years of age
- with any other product containing diphenhydramine, even one used on skin

Ask a doctor before use if you have

- a breathing problem such as emphysema or chronic bronchitis
- glaucoma
- trouble urinating due to an enlarged prostate gland

Ask a doctor or pharmacist before use if you are

taking sedatives or tranquilizer.

When using this product,

avoid alcoholic beverages.

Stop use and ask a doctor if

sleeplessness persists continuously for more than 2 weeks. Insomnia may be a symptom of a serious underlying medical illness.

If pregnant or breast-feeding,

ask a health professional before use.

Keep out of reach of children.

In case of overdose, get medical help or contact a Poison Control Center (1-800-222-1222) right away.

Directions

- take only one dose per day (24 hours)
- mL=milliliter
- keep dosing cup with product
- measure only with dosing cup provided. Do not use any other dosing device.
- adults and children 12 years and over
  - one dose=30 mL at bedtime if needed, or as directed by a doctor
- children under 12 years: do not use

Other information

- each 30 mL contains: sodium 23 mg
- store between 20-25ºC (68-77ºF). Do not refrigerate.
- protect from light

Inactive ingredients

citric acid, ethyl alcohol, FD&C blue #1, FD&C red #40, flavor, high fructose corn syrup, polyoxyl 40 stearate, propylene glycol, purified water, saccharin sodium , sodium benzoate, sodium citrate

Questions or comments?

Call 1-877-753-3935 Monday-Friday 9AM-5PM EST

Principal Display Panel

Compare to the active ingredient in ZzzQuil®*

ez nite

sleep aid

diphenhydramine HCI 50 mg

nighttime sleep-aid

- not for treating cold or flu
- alcohol 10%

berry flavor

fl oz (mL)

Failure to follow these warnings could result in serious consequences.

*This product is not manufactured or distributed by The Procter & Gamble Company. ZzzQuil® is a registered trademark of The Procter & Gamble Company.

TAMPER EVIDENT: DO NOT USE IF PRINTED SAFETY SEAL AROUND DOSAGE CUP OR UNDER CAP IS BROKEN OR MISSING.

Manufactured by:

PL Developments

11865 S. Alameda St

Lynwood, CA 90262

Package Label

READYinCASE Nighttime Sleep Aid Berry Flavor